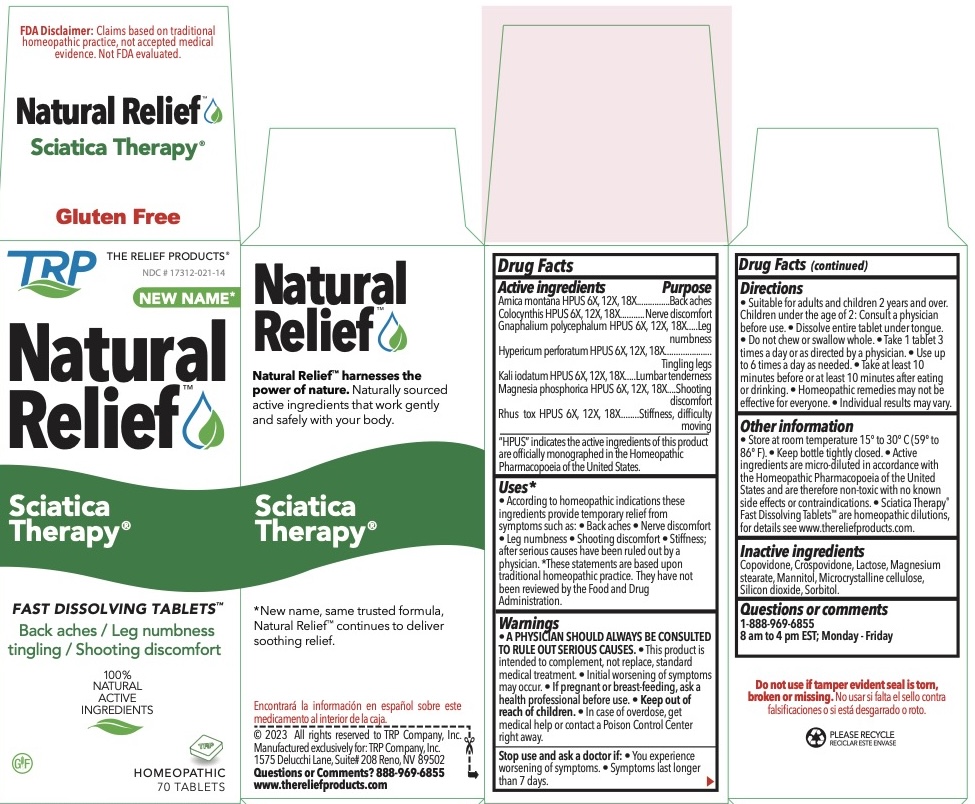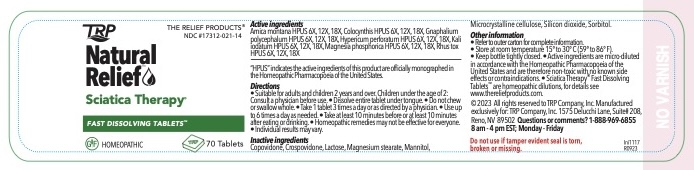 DRUG LABEL: Sciatica Therapy
NDC: 17312-021 | Form: TABLET, ORALLY DISINTEGRATING
Manufacturer: TRP Company
Category: homeopathic | Type: HUMAN OTC DRUG LABEL
Date: 20251215

ACTIVE INGREDIENTS: ARNICA MONTANA 6 [hp_X]/1 1; CITRULLUS COLOCYNTHIS FRUIT PULP 6 [hp_X]/1 1; PSEUDOGNAPHALIUM OBTUSIFOLIUM 6 [hp_X]/1 1; HYPERICUM PERFORATUM 6 [hp_X]/1 1; POTASSIUM IODIDE 6 [hp_X]/1 1; MAGNESIUM PHOSPHATE, DIBASIC TRIHYDRATE 6 [hp_X]/1 1; TOXICODENDRON PUBESCENS LEAF 6 [hp_X]/1 1
INACTIVE INGREDIENTS: SORBITOL; CROSPOVIDONE; CELLULOSE, MICROCRYSTALLINE; COPOVIDONE; SILICON DIOXIDE; LACTOSE; MAGNESIUM STEARATE; MANNITOL

Sciatica Therapy™ Homeopathic Fast Dissolving Tablets

Active Ingredients |  | Purpose
Arnica Montana HPUS | 6x, 12x, 18x | Back aches
Colocynthis HPUS | 6x, 12x, 18x | Nerve discomfort
Gnaphalium polycephalum HPUS | 6X, 12x, 18x | Leg numbness
Hypericum perforatum HPUS | 6X, 12x, 18x | Tingling legs
Kali iodatum HPUS | 6X, 12x, 18x | Lumbar tenderness
Magnesia phosphorica HPUS | 6X, 12x, 18x | Shooting discomfort
Rhus toxicodendron HPUS | 6X, 12x, 18x | Stiffness, Difficulty moving

The letters HPUS indicate that the components of this product are officially monographed in the Homeopathic Pharmacopoeia of the United States.

Uses:
According to homeopathic indications these ingredients provide temporary relief from symptoms of Sciatica such as: • back aches • nerve discomfort • leg numbness • tingling legs • shooting discomfort • stiffness • tearing pain after serious causes have been ruled out by a physician.

* These statements are based upon traditional homeopathic practice. They have not been reviewed by the Food and Drug Administration.

Warnings:
A PHYSICIAN SHOULD ALWAYS BE CONSULTED TO RULE OUT SERIOUS CAUSES.

- This product is intended to complement, not replace, standard medical treatment.
- Initial worsening of symptoms may occur.
- A physician should always be consulted regarding Sciatica to rule out serious causes.
- In case of overdose, get medical help or contact a Poison Control Center right away.

Stop use and ask a doctor if: • Symptoms persist for more than 7 days or worsen, if new symptoms occur or if redness or swelling is present because these could be a sign of a serious illness.

Keep out of reach of children

PREGNANCY OR BREAST FEEDING

If pregnant or breast-feeding, ask a health professional before use.

Directions:

- Suitable for adults and children ages 2 and over.
- Children under the age of 2: consult a physician before use.
- Dissolve entire tablet under tongue.
- Do not chew or swallow whole.
- Take 1 tablet 3 times a day or as directed by a physician.
- Use up to 6 times a day as needed.
- Take at least 10 minutes before or at least 10 minutes after eating or drinking.

Other information:

- Active ingredients are micro-diluted in accordance with the Homeopathic Pharmacopoeia of the United States and are therefore non-toxic with no known side effects.
- Store in a cool dark location.

Inactive Ingredients:
Advantol® 300, Lactose, Magnesium Stearate, Mannitol, Microcrystalline Cellulose.

QUESTIONS

For more information and to order related products call toll free: 888-969-6855 or trpcompany.com